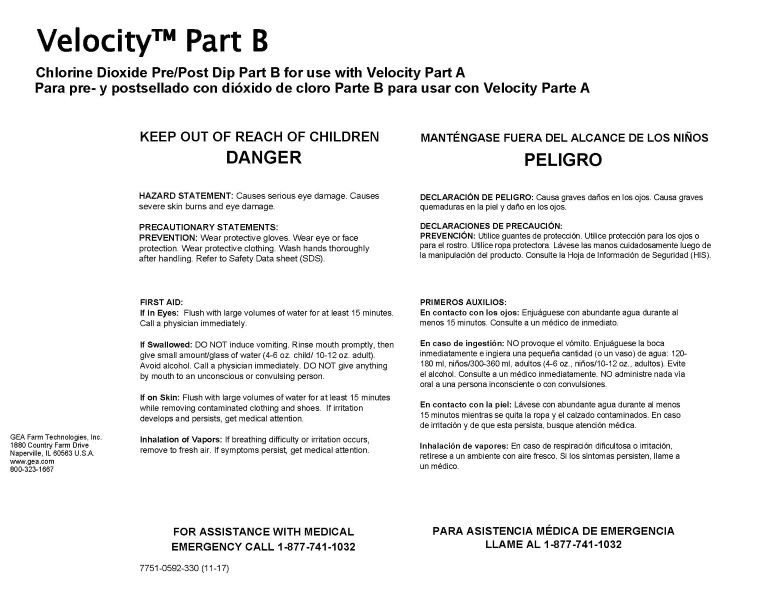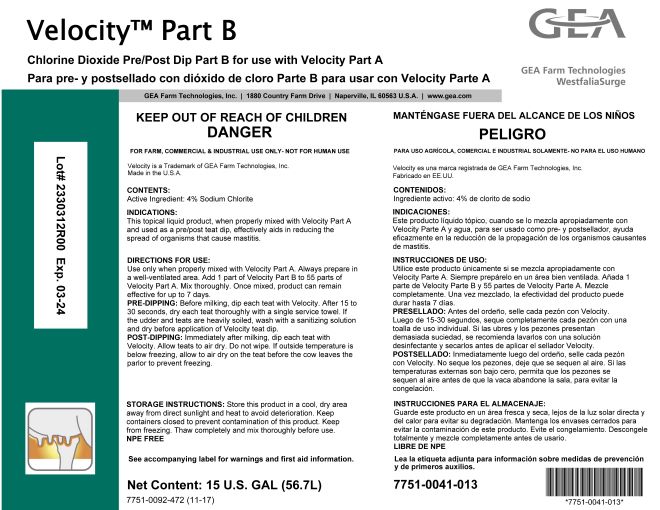 DRUG LABEL: GEA Velocity Part B
NDC: 51070-7011 | Form: LIQUID
Manufacturer: GEA Farm Technologies, Inc.
Category: animal | Type: OTC ANIMAL DRUG LABEL
Date: 20240605

ACTIVE INGREDIENTS: SODIUM CHLORITE 4.2 g/100 g
INACTIVE INGREDIENTS: EDETATE SODIUM; SODIUM GLUCONATE

Velocity Part B

ACTIVE INGREDIENT

CONTENTS:

ACTIVE INGREDIENT: 4% Sodium Chlorite

Net Content: 15 U.S. GAL (56.7L)

KEEP OUT OF REACH OF CHILDREN

DANGER

PRECAUTIONS

HAZARD STATEMENT: Causes serious eye damage. Causes severe skin burns and eye damage.

PRECAUTIONARY STATEMENTS:

PREVENTION: Wear protective gloves. Wear eye or face protection. Wear protective clothing. Wash hands thoroughly after handling. Refer to Safety Data sheet (SDS).

USER SAFETY WARNINGS

FIRST AID:

If in Eyes: Flush with large volumes of water for at least 15 minutes. Call a physician immediately.
If Swallowed: DO NOT induce vomiting. Rinse mouth promptly, then give small amount/glass of water (4-6 oz. child / 10-12 oz. adult). Avoid alcohol. Call a physician immediately. DO NOT give anything by mouth to an unconscious or convulsing person.
If on Skin: Flush with large volumes of water for at least 15 minutes while removing contaminated clothing and shoes. If irritation develops and persists, get medical attention.
Inhalation of Vapors: If breathing difficulty or irritation occurs, remove to fresh air. If symptoms persist, get medical attention.

FOR ASSISTANCE WITH MEDICAL EMERGENCY

CALL 1-877-741-1032

FOR FARM, COMMERCIAL & INDUSTRIAL USE ONLY- NOT FOR HUMAN USE

Velocity is a Trademark of GEA Farm Technologies, Inc.

Made in U.S.A.

INDICATIONS AND USAGE

INDICATIONS: This topical liquid product, when properly mixed with Velocity Part A and used as a pre/post teat dip, effectively aids in reducing the spread of organisms that cause mastitis.

DOSAGE AND ADMINISTRATION

DIRECTIONS FOR USE: Use only when properly mixed with Velocity Part A. Always prepare mixture in a well-ventilated area. Add 1 part of Velocity Part B to 55 parts of Velocity Part A. Mix thoroughly. Once mixed, product can remain effective for up to 7 days.

PRE-DIPPING: Before milking, dip each teat with Velocity. After 15 to 30 seconds, dry each treat thoroughly with a single service towel. If the udder and teats are heavily soiled, wash with a sanitizing solution and dry before application of Velocity teat dip.

POST-DIPPING: Immediately after milking, dip each teat with Velocity. Allow teats to air dry. Do not wipe. If outside temperature is below freezing, allow to air dry on the teat before the cow leaves the parlor to prevent freezing.

STORAGE INSTRUCTIONS:

Store this product in a cool, dry area away from direct sunlight and heat to avoid deterioration. Keep containers closed to prevent contamination of this product. Keep from freezing. Thaw completely and mix thoroughly before use.

NPE FREE

See accompanying label for warnings and first aid information.

7751-0092-472 (11-17)

GEA Farm Technologies, Inc. • 1880 Country Farm Drive • Naperville, IL 60563 U.S.A • www.gea.com

7751-0041-013

GEA Farm Technologies, Inc.

1880 Country Farm Dr.

Naperville, IL 60563 U.S.A.

www.gea.com

800-323-1667

7751-0592-330 (11-17)

PACKAGE LABEL

Velocity™ Part B

Chlorine Dioxide Pre/Post Dip Part A for use with Velocity Part B